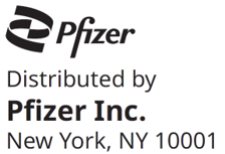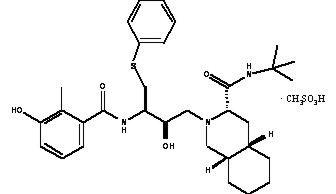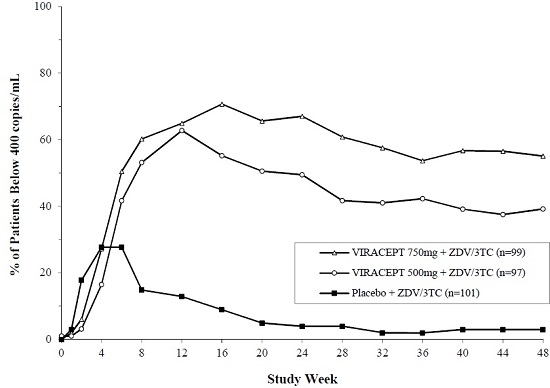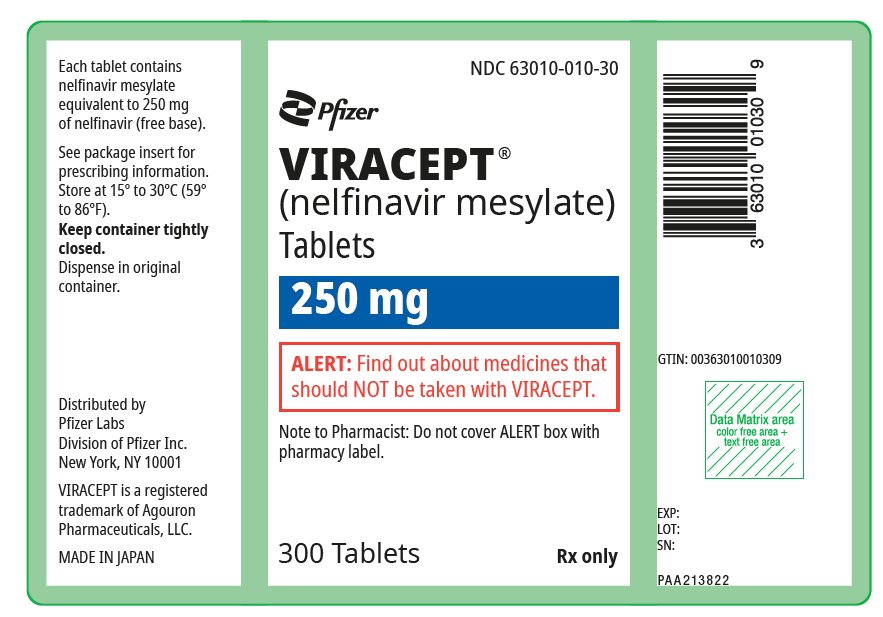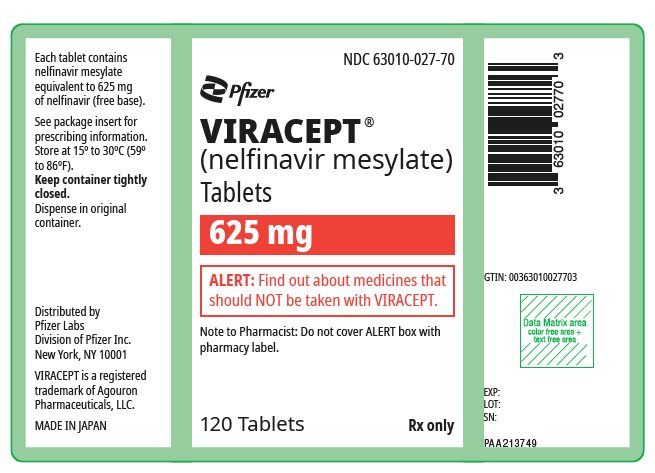 DRUG LABEL: VIRACEPT
NDC: 63010-010 | Form: TABLET, FILM COATED
Manufacturer: AGOURON
Category: prescription | Type: HUMAN PRESCRIPTION DRUG LABEL
Date: 20251211

ACTIVE INGREDIENTS: NELFINAVIR MESYLATE 250 mg/1 1
INACTIVE INGREDIENTS: CALCIUM SILICATE; CROSPOVIDONE (120 .MU.M); MAGNESIUM STEARATE; HYPROMELLOSE, UNSPECIFIED; TRIACETIN; FD&C BLUE NO. 2

HIGHLIGHTS OF PRESCRIBING INFORMATION

These highlights do not include all the information needed to use VIRACEPT safely and effectively. See full prescribing information for VIRACEPT.
VIRACEPT® (nelfinavir mesylate) Tablets, for oral use
VIRACEPT® (nelfinavir mesylate) Oral Powder, for oral use
Initial U.S. Approval: 1997

1 INDICATIONS AND USAGE

VIRACEPT is a protease inhibitor indicated for the treatment of HIV-1 infection in combination with other antiretroviral agents. (1)

2 DOSAGE AND ADMINISTRATION

- See full prescribing information for administration instructions (2)
- Adults and adolescents 13 years and older (tablets): 1250 mg twice daily or 750 mg three times daily with a meal (2.1)
- Children 2 to less than 13 years (oral powder or 250 mg tablets): 45 to 55 mg/kg twice daily or 25 to 35 mg/kg three times daily with a meal. Refer to Tables 1 and 2 of the full prescribing information for specific dosing guidelines based on age and body weight (2.2)

3 DOSAGE FORMS AND STRENGTHS

- Tablet: 250 mg, 625 mg nelfinavir free base (3)
- Oral Powder: 50 mg/g nelfinavir free base (3)

4 CONTRAINDICATIONS

- Coadministration with drugs that are highly dependent on CYP3A for clearance and which elevated concentrations are associated with serious and/or life-threatening events (4)

5 WARNINGS AND PRECAUTIONS

ALERT: Find out about medicines that should not be taken with VIRACEPT.

- The concomitant use of VIRACEPT and certain other drugs may result in known or potentially significant drug interactions. Consult the full prescribing information prior to and during treatment for potential drug interactions (5.1, 7.3)
- Hepatic impairment: should not be used in patients with either moderate or severe hepatic impairment (2.4, 5.2)
- Phenylketonuria: the oral powder contains 11.2 mg phenylalanine per gram of powder (5.3)
- Diabetes mellitus/hyperglycemia: new onset or exacerbation of pre-existing diabetes mellitus and hyperglycemia reported with protease inhibitors. In some cases after treatment discontinuation, hyperglycemia persisted (5.4)
- Hemophilia: increased bleeding, including spontaneous skin hematomas and hemarthrosis reported with protease inhibitors. In more than half of the cases, protease inhibitors was continued or reintroduced (5.5)
- Fat redistribution: observed with antiretroviral therapy (5.6)
- Immune reconstitution syndrome: reported with combination antiretroviral therapy, including VIRACEPT. Patients may develop an inflammatory response to indolent or residual opportunistic infections (5.7)

6 ADVERSE REACTIONS

- Most common adverse reactions (≥2%) of moderate or severe intensity in adults and adolescents (13 years and older) are diarrhea, nausea, rash, and flatulence (6.1)
- Most common adverse reactions in pediatric patients (2 to less than 13 years) are diarrhea, leukopenia/neutropenia, rash, anorexia, and abdominal pain. (6.2)

To report SUSPECTED ADVERSE REACTIONS, contact Pfizer Inc at 1-800-438-1985 or FDA at 1-800-FDA-1088 or www.fda.gov/medwatch.

7 DRUG INTERACTIONS

- Coadministration of VIRACEPT with other drugs (CYP3A substrates) can alter the concentration of these other drugs, and other drugs (inhibitors and/or inducers of CYP3A or CYP2C19) may alter the concentrations of nelfinavir. The potential drug-drug concentrations must be considered prior to and during therapy (4, 7, 12.3)
- VIRACEPT should be given with food one hour after or more than 2 hours before didanosine (7)

8 USE IN SPECIFIC POPULATIONS

- Use during pregnancy if the potential benefit justifies the potential risk to the fetus (8.1)
- Lactation: Patients infected with HIV should be instructed not to breastfeed due to the potential for HIV transmission (8.2)

FULL PRESCRIBING INFORMATION

1 INDICATIONS AND USAGE

VIRACEPT in combination with other antiretroviral agents is indicated for the treatment of HIV-1 infection.

2 DOSAGE AND ADMINISTRATION

2.1 Adults and Adolescents (13 years and older)

The recommended dose is 1250 mg (five 250 mg tablets or two 625 mg tablets) twice daily or 750 mg (three 250 mg tablets) three times daily. VIRACEPT should be taken with a meal. Patients unable to swallow the 250 or 625 mg tablets may dissolve the tablets in a small amount of water [see Dosage and Administration (2.3)].

2.2 Pediatric Patients (2 to less than 13 years)

In children 2 years of age and older, the recommended oral dose of VIRACEPT Oral Powder or 250 mg tablets is 45 to 55 mg/kg twice daily or 25 to 35 mg/kg three times daily. All doses should be taken with a meal. Doses higher than the adult maximum dose of 2500 mg per day have not been studied in children.

For children unable to swallow tablets, VIRACEPT 250 mg tablet(s) may be dissolved in a small amount of water or, VIRACEPT Oral Powder may be administered [see Dosage and Administration (2.3)].

The healthcare provider should assess appropriate formulation and dosage for each patient. Tables 1 and 2 provide dosing guidelines for VIRACEPT tablets and powder based on age and body weight.

Table 1: Dosing Table for Children 2 to less than 13 years of age (tablets)
Body weight | Twice daily (BID) 45 – 55 mg/kg ≥2 years | Three times daily (TID) 25 – 35 mg/kg ≥2 years
Body weight | Number of tablets (250 mg) | Number of tablets (250 mg)
Kg
10 – 12 | 2 | 1
13 – 18 | 3 | 2
19 – 20 | 4 | 2
≥21 | 4 – 5 [For BID dosing, the maximum dose per day is 5 tablets BID] | 3 [For TID dosing, the maximum dose per day is 3 tablets TID]

Table 2: Dosing Table for Children 2 to less than 13 years of age (powder)
Body weight | Twice daily (BID) 45 – 55 mg/kg |  | Three times daily (TID) 25 – 35 mg/kg
Kg | Scoops of powder (50 mg/1 g) | Teaspoons [If a teaspoon is used to measure VIRACEPT oral powder, 1 level teaspoon contains 200 mg of VIRACEPT (4 level scoops equals 1 level teaspoon)] of powder | Scoops of powder (50 mg/1 g) | Teaspoons of powder
9.0 to <10.5 | 10 | 2½ | 6 | 1½
10.5 to <12 | 11 | 2¾ | 7 | 1¾
12 to <14 | 13 | 3¼ | 8 | 2
14 to <16 | 15 | 3¾ | 9 | 2¼
16 to <18 | Not recommended [Use VIRACEPT 250 mg tablet] | Not recommended | 10 | 2½
18 to <23 | Not recommended | Not recommended | 12 | 3
≥23 | Not recommended | Not recommended | 15 | 3¾

2.3 Method of Administration

For Patients Unable to Swallow Viracept Tablets

- Place VIRACEPT tablet(s) in small amount of water.
- Once dissolved, mix the cloudy liquid well, and consume it immediately.
- The glass should be rinsed with water and the rinse swallowed to ensure the entire dose is consumed.

Viracept Oral Powder

- Mix VIRACEPT Oral Powder with a small amount of water, milk, formula, soy formula, soy milk, or dietary supplements
- Once mixed, the entire contents must be consumed in order to obtain the full dose.
- If the mixture is not consumed immediately, it must be stored under refrigeration, but storage must not exceed 6 hours.
- Acidic food or juice (e.g., orange juice, apple juice, or apple sauce) are not recommended for mixing VIRACEPT Oral Powder because the combination may result in a bitter taste.
- VIRACEPT Oral Powder should not be reconstituted with water in its original container.

2.4 Hepatic Impairment

VIRACEPT can be used in patients with mild hepatic impairment without any dose adjustment. VIRACEPT should not be used in patients with either moderate or severe hepatic impairment [see Warnings and Precautions (5.2), Use in Specific Populations (8.6), and Clinical Pharmacology (12.3)].

3 DOSAGE FORMS AND STRENGTHS

VIRACEPT 250 mg Tablet: Light-blue, capsule-shaped tablets with a clear film coating engraved with "VIRACEPT" on one side and "250 mg" on the other.

VIRACEPT 625 mg Tablet: White oval tablet with a clear film coating engraved with "V" on one side and "625" on the other.

VIRACEPT Oral Powder: Off-white powder containing 50 mg (as nelfinavir-free base) in each level scoopful (1 gram).

4 CONTRAINDICATIONS

Coadministration of VIRACEPT is contraindicated with drugs that are highly dependent on CYP3A for clearance and for which elevated plasma concentrations are associated with serious and/or life-threatening events. These drugs and other contraindicated drugs (which may lead to reduced efficacy of nelfinavir) are listed in Table 3 [also see Drug Interactions (7), Table 6].

Table 3: Drugs That Are Contraindicated With VIRACEPT
Drug Class | Drugs Within Class That Are Contraindicated With VIRACEPT | Clinical Comment
Alpha 1-adrenoreceptor antagonist | Alfuzosin | Potentially increased alfuzosin concentrations can result in hypotension.
Antiarrhythmics | Amiodarone, quinidine | Potential for serious and/or life-threatening cardiac arrhythmia.
Antimycobacterial Agents | Rifampin | Plasma concentrations of nelfinavir can be reduced by concomitant use of rifampin. This may lead to loss of therapeutic effect and possible development of resistance to VIRACEPT or other coadministered antiretroviral agents.
Antipsychotics | Lurasidone; Pimozide | Potential for serious and/or life-threatening reactions. Potential for serious and/or life threatening reactions such as cardiac arrhythmias.
Ergot Derivatives | Dihydroergotamine, ergotamine, methylergonovine | Potential for serious and/or life threatening reactions such as ergot toxicity characterized by peripheral vasospasm and ischemia of the extremities and other tissues.
GI Motility Agent | Cisapride | Potential for serious and/or life threatening reactions such as cardiac arrhythmias.
Herbal products | St. John's wort (Hypericum perforatum) | Plasma concentrations of nelfinavir can be reduced by concomitant use of the herbal preparation St. John's wort. This may lead to loss of therapeutic effect and possible development of resistance to VIRACEPT or other coadministered antiretroviral agents.
HMG-CoA Reductase Inhibitors | Lovastatin, Simvastatin | Potential for serious reactions such as myopathy including rhabdomyolysis.
PDE5 Inhibitors | Sildenafil (Revatio®) [for treatment of pulmonary arterial hypertension] [See Drug Interactions, Table 6 for coadministration of sildenafil and tadalafil when dosed for erectile dysfunction.] | A safe and effective dose has not been established when used with nelfinavir. There is increased potential for sildenafil-associated adverse events (which include visual disturbances, hypotension, prolonged erection, and syncope).
Sedative/Hypnotics | Triazolam, oral midazolam | Potential for serious and/or life threatening reactions such as prolonged or increased sedation or respiratory depression.

5 WARNINGS AND PRECAUTIONS

ALERT: Find out about medicines that should not be taken with VIRACEPT. This statement is included on the product's bottle label.

5.1 Risk of Serious Adverse Reactions Due to Drug Interactions

Initiation of VIRACEPT, a CYP3A inhibitor, in patients receiving medications metabolized by CYP3A or initiation of medications metabolized by CYP3A in patients already receiving VIRACEPT, may increase plasma concentrations of medications metabolized by CYP3A. Initiation of medications that inhibit or induce CYP3A may increase or decrease concentrations of VIRACEPT, respectively. These interactions may lead to:

- Clinically significant adverse reactions, potentially leading to severe, life threatening, or fatal events from greater exposures of concomitant medications.
- Clinically significant adverse reactions from greater exposures of VIRACEPT.
- Loss of therapeutic effect of VIRACEPT and possible development of resistance.

See Table 6 for steps to prevent or manage these possible and known significant drug interactions, including dosing recommendations [see Drug Interactions (7)]. Consider the potential for drug interactions prior to and during VIRACEPT therapy; review concomitant medications during VIRACEPT therapy; and monitor for the adverse reactions associated with the concomitant medications [see Contraindications (4) and Drug Interactions (7)].

5.2 Hepatic Impairment

VIRACEPT should not be used in patients with either moderate or severe hepatic impairment (Child-Pugh B or C, score greater than or equal to 7) [see Dosage and Administration (2.4) and Clinical Pharmacology (12.3)].

5.3 Phenylketonurics

Viracept Oral Powder contains phenylalanine, a component of aspartame. Each gram of VIRACEPT powder contains 11.2 mg phenylalanine. Phenylalanine can be harmful to patients with phenylketonuria.

5.4 Diabetes Mellitus/Hyperglycemia

New onset diabetes mellitus, exacerbation of pre-existing diabetes mellitus and hyperglycemia have been reported during post-marketing surveillance in HIV-infected patients receiving protease inhibitor therapy. Some patients required either initiation or dose adjustments of insulin or oral hypoglycemic agents for treatment of these events. In some cases diabetic ketoacidosis has occurred. In those patients who discontinued protease inhibitor therapy, hyperglycemia persisted in some cases. Because these events have been reported voluntarily during clinical practice, estimates of frequency cannot be made and a causal relationship between protease inhibitor therapy and these events has not been established.

5.5 Hemophilia

There have been reports of increased bleeding, including spontaneous skin hematomas and hemarthrosis, in patients with hemophilia type A and B treated with protease inhibitors. In some patients, additional factor VIII was given. In more than half of the reported cases, treatment with protease inhibitors was continued or reintroduced. A causal relationship has not been established.

5.6 Fat Redistribution

Redistribution/accumulation of body fat including central obesity, dorsocervical fat enlargement ("buffalo hump"), peripheral wasting, facial wasting, breast enlargement, and "cushingoid appearance" have been observed in patients receiving antiretroviral therapy. The mechanism and long-term consequences of these events are currently unknown. A causal relationship has not been established.

5.7 Immune Reconstitution Syndrome

Immune reconstitution syndrome has been reported in patients treated with combination antiretroviral therapy, including VIRACEPT. During the initial phase of combination antiretroviral treatment, patients whose immune system responds may develop an inflammatory response to indolent or residual opportunistic infections [such as Mycobacterium avium infection, cytomegalovirus, Pneumocystis jiroveci pneumonia (PCP), or tuberculosis], which may necessitate further evaluation and treatment.

Autoimmune disorders (such as Graves' disease, polymyositis, and Guillain-Barré syndrome) have also been reported to occur in the setting of immune reconstitution; however, the time to onset is more variable, and can occur many months after initiation of treatment.

6 ADVERSE REACTIONS

Because clinical trials are conducted under widely varying conditions, adverse reaction rates observed in the clinical trials of a drug cannot be directly compared to rates in the clinical trials of another drug and may not reflect the rates observed in practice.

6.1 Clinical Trials Experience: Adults and Adolescents (13 years and older)

The safety of VIRACEPT was studied in over 5000 patients who received drug either alone or in combination with nucleoside analogues. The majority of adverse events were of mild intensity. The most frequently reported adverse event among patients receiving VIRACEPT was diarrhea, which was generally of mild to moderate intensity.

Drug-related clinical adverse experiences of moderate or severe intensity in ≥2% of patients treated with VIRACEPT coadministered with d4T and 3TC (Study 542) for up to 48 weeks, or with ZDV plus 3TC (Study 511) for up to 24 weeks are presented in Table 4.

Table 4: Percentage of Patients with Treatment-Emergent [Includes those adverse events at least possibly, probably or definitely related to study drug or of unknown relationship and excludes concurrent HIV conditions] Adverse Events of Moderate or Severe Intensity Reported in ≥ 2% of Adult and Adolescent Patients
 | Study 511 |  |  | Study 542
 | 24 weeks |  |  | 48 weeks
Adverse Events | Placebo + ZDV/3TC (n=101) | 500 mg TID VIRACEPT + ZDV/3TC (n=97) | 750 mg TID VIRACEPT + ZDV/3TC (n=100) | 1250 mg BID VIRACEPT + d4T/3TC (n=344) | 750 mg TID VIRACEPT + d4T/3TC (n=210)
Digestive System
Diarrhea | 3% | 14% | 20% | 20% | 15%
Nausea | 4% | 3% | 7% | 3% | 3%
Flatulence | 0 | 5% | 2% | 1% | 1%
Skin/Appendages
Rash | 1% | 1% | 3% | 2% | 1%

Adverse events occurring in less than 2% of patients receiving VIRACEPT in all phase 2 and 3 clinical trials and considered at least possibly related or of unknown relationship to treatment and of at least moderate severity are listed below.

Body as a Whole: abdominal pain, accidental injury, allergic reaction, asthenia, back pain, fever, headache, malaise, pain, and redistribution/accumulation of body fat [see Warnings and Precautions (5.7)].

Digestive System: anorexia, dyspepsia, epigastric pain, gastrointestinal bleeding, hepatitis, mouth ulceration, pancreatitis, and vomiting.

Hemic/Lymphatic System: anemia, leukopenia, and thrombocytopenia.

Metabolic/Nutritional System: increases in alkaline phosphatase, amylase, creatine phosphokinase, lactic dehydrogenase, SGOT, SGPT, and gamma-glutamyl transpeptidase; hyperlipemia, hyperuricemia, hyperglycemia, hypoglycemia, dehydration, and liver function tests abnormal.

Musculoskeletal System: arthralgia, arthritis, cramps, myalgia, myasthenia, and myopathy.

Nervous System: anxiety, depression, dizziness, emotional lability, hyperkinesia, insomnia, migraine, paresthesia, seizures, sleep disorder, somnolence, and suicide ideation.

Respiratory System: dyspnea, pharyngitis, rhinitis, and sinusitis.

Skin/Appendages: dermatitis, folliculitis, fungal dermatitis, maculopapular rash, pruritus, sweating, and urticaria.

Special Senses: acute iritis and eye disorder.

Urogenital System: kidney calculus, sexual dysfunction, and urine abnormality.

Laboratory Abnormalities

The percentage of patients with marked laboratory abnormalities in Studies 542 and 511 are presented in Table 5. Marked laboratory abnormalities are defined as a Grade 3 or 4 abnormality in a patient with a normal baseline value, or a Grade 4 abnormality in a patient with a Grade 1 abnormality at baseline.

Table 5: Percentage of Patients by Treatment Group with Marked Laboratory Abnormalities [Marked laboratory abnormalities are defined as a shift from Grade 0 at baseline to at least Grade 3 or from Grade 1 to Grade 4] in >2% of Patients
 | Study 511 |  |  | Study 542
 | Placebo + ZDV/3TC (n=101) | 500 mg TID VIRACEPT + ZDV/3TC (n=97) | 750 mg TID VIRACEPT + ZDV/3TC (n=100) | 1250 mg BID VIRACEPT + d4T/3TC (n=344) | 750 mg TID VIRACEPT + d4T/3TC (n=210)
Hematology
Hemoglobin | 6% | 3% | 2% | 0 | 0
Neutrophils | 4% | 3% | 5% | 2% | 1%
Lymphocytes | 1% | 6% | 1% | 1% | 0
Chemistry
ALT (SGPT) | 6% | 1% | 1% | 2% | 1%
AST (SGOT) | 4% | 1% | 0 | 2% | 1%
Creatine Kinase | 7% | 2% | 2% | NA | NA

6.2 Clinical Trials Experience: Pediatrics (2 to less than 13 years of age)

VIRACEPT has been studied in approximately 400 pediatric patients in clinical trials from birth to 13 years of age. The adverse event profile seen during pediatric clinical trials was similar to that for adults.

The most commonly reported drug-related, treatment-emergent adverse events reported in the pediatric studies included: diarrhea, leukopenia/neutropenia, rash, anorexia, and abdominal pain. Diarrhea, regardless of assigned relationship to study drug, was reported in 39% to 47% of pediatric patients receiving VIRACEPT in 2 of the larger treatment trials. Leukopenia/neutropenia was the laboratory abnormality most commonly reported as a significant event across the pediatric studies.

6.3 Postmarketing Experience

The following adverse reactions have been identified during post-approval use of VIRACEPT. Because these reactions are reported voluntarily from a population of uncertain size, it is not always possible to reliably estimate their frequency or establish a causal relationship to drug exposure.

Body as a Whole: hypersensitivity reactions (including bronchospasm, moderate to severe rash, fever, and edema).

Cardiovascular System: QTc prolongation, torsades de pointes.

Digestive System: jaundice.

Metabolic/Nutritional System: bilirubinemia, metabolic acidosis.

7 DRUG INTERACTIONS

7.1 Potential for VIRACEPT to Affect Other Drugs

Nelfinavir is an inhibitor of CYP3A. Coadministration of VIRACEPT and drugs primarily metabolized by CYP3A (e.g., dihydropyridine calcium channel blockers, HMG-CoA reductase inhibitors, immunosuppressants, and PDE5 inhibitors) may result in increased plasma concentrations of such drugs that could increase or prolong both its therapeutic and adverse effects (see Tables 3 and 6).

7.2 Potential for Other Drugs to Affect VIRACEPT

Nelfinavir is metabolized by CYP3A and CYP2C19. Coadministration of VIRACEPT and drugs that induce CYP3A or CYP2C19, such as rifampin, may decrease nelfinavir plasma concentrations and reduce its therapeutic effect. Coadministration of VIRACEPT and drugs that inhibit CYP3A or CYP2C19 may increase nelfinavir plasma concentrations.

7.3 Established and Other Potentially Significant Drug Interactions

Table 6 provides the effect on concentrations of VIRACEPT or concomitant drug as a result of coadministration with VIRACEPT. These recommendations are based on either drug interaction studies or predicted interactions due to the expected magnitude of interaction and potential for serious adverse events or loss of efficacy.

Table 6: Established and Other Potentially Significant Drug Interactions: Alteration in Dose or Regimen May Be Recommended Based on Drug Interaction Studies [see Clinical Pharmacology (12.3) (Tables 12 and 13) for magnitude of interaction]

Concomitant Drug Class: Drug Name | Effect on Concentration | Clinical Comment
HIV Antiviral Agents: Reverse Transcriptase Inhibitors
Delavirdine | ↑ nelfinavir (Cmin) ↓ delavirdine | Concentrations of nelfinavir were increased while concentrations of delavirdine were decreased when the two agents were coadministered. Appropriate doses of the combination, with respect to safety and efficacy, have not been established.
Nevirapine | ↓ nelfinavir (Cmin) | Concentrations of nelfinavir were decreased when coadministered with nevirapine. An appropriate dose of nelfinavir with respect to safety and efficacy has not been established.
Didanosine | ↔ nelfinavir | There was no change in nelfinavir concentration when coadministered with didanosine. However, it is recommended that didanosine be administered on an empty stomach; therefore, didanosine should be given one hour before or two hours after VIRACEPT (given with food).
HIV Antiviral Agents: Protease Inhibitors
Indinavir | ↑ nelfinavir ↑ indinavir | Concentrations of both indinavir and nelfinavir were increased when the two agents were coadministered. Appropriate doses for these combinations, with respect to safety and efficacy, have not been established.
Ritonavir | ↑ nelfinavir ↔ ritonavir | Concentrations of nelfinavir were increased when coadministered with ritonavir. An appropriate dose of nelfinavir for this combination, with respect to safety and efficacy, has not been established.
Saquinavir | ↑ nelfinavir ↑ saquinavir | Concentrations of both saquinavir and nelfinavir were increased when the two agents were coadministered. Appropriate doses for these combinations, with respect to safety and efficacy, have not been established.
ANTICOAGULANT
Warfarin | Warfarin | Coadministration of warfarin and VIRACEPT may affect concentrations of warfarin. It is recommended that the INR (international normalized ratio) be monitored carefully during treatment with VIRACEPT, especially when commencing therapy.
ANTICONVULSANTS
Carbamazepine Phenobarbital Phenytoin | ↓ nelfinavir ↓ phenytoin | Concentrations of nelfinavir may be decreased. VIRACEPT may not be effective due to decreased nelfinavir plasma concentrations in patients taking these agents concomitantly. Phenytoin plasma/serum concentrations should be monitored; phenytoin dose may require adjustment to compensate for altered phenytoin concentration.
ANTIDEPRESSANT
Trazodone | ↑ trazodone | Concomitant use of trazodone and VIRACEPT may increase plasma concentrations of trazodone. Adverse events of nausea, dizziness, hypotension and syncope have been observed following coadministration of trazodone and ritonavir. If trazodone is used with a CYP3A4 inhibitor such as VIRACEPT, the combination should be used with caution and a lower dose of trazodone should be considered.
ANTIGOUT
Colchicine | ↑ colchicines | Patients with renal or hepatic impairment should not be given colchicine with VIRACEPT due to the risk of colchicine toxicity. Treatment of gout flares – co- administration of colchicine in patients on VIRACEPT: 0.6 mg (1 tablet) × 1 dose, followed by 0.3 mg (half tablet) 1 hour later. Dose to be repeated no earlier than 3 days. Prophylaxis of gout-flares – coadministration of colchicine in patients on VIRACEPT: If the original colchicine regimen was 0.6 mg twice a day, the regimen should be adjusted to 0.3 mg once a day. If the original colchicine regimen was 0.6 mg once a day, the regimen should be adjusted to 0.3 mg once every other day. Treatment of familial Mediterranean fever (FMF)– coadministration of colchicine in patients on VIRACEPT: Maximum daily dose of 0.6 mg (may be given as 0.3 mg twice a day).
ANTIMYCOBACTERIAL
Rifabutin | ↑ rifabutin ↓ nelfinavir (750 mg TID) ↔ nelfinavir (1250 mg BID) | It is recommended that the dose of rifabutin be reduced to one-half the usual dose when administered with VIRACEPT; 1250 mg BID is the preferred dose of VIRACEPT when coadministered with rifabutin.
ENDOTHELIN RECEPTOR ANTAGONIST
Bosentan | ↑ bosentan | Concentrations of bosentan may be increased when coadministered with VIRACEPT. Coadministration of bosentan in patients on VIRACEPT or coadministration of VIRACEPT in patients on bosentan: Start at or adjust bosentan to 62.5 mg once daily or every other day based upon individual tolerability.
HMG-CoA REDUCTASE INHIBITORS
Atorvastatin Rosuvastatin | ↑ atorvastatin ↑ rosuvastatin | Titrate atorvastatin dose carefully and use the lowest necessary dose; do not exceed atorvastatin 40 mg/day.
IMMUNOSUPPRESSANTS
Cyclosporine Tacrolimus Sirolimus | ↑ immuno-suppressants ↑ nelfinavir | Concentrations of these immunosuppressants and nelfinavir may be increased by coadministration of these agents with nelfinavir.
INHALED BETA AGONIST
Salmeterol | ↑ salmeterol | Concurrent administration of salmeterol with VIRACEPT is not recommended. The combination may result in increased risk of cardiovascular adverse events associated with salmeterol, including QT prolongation, palpitations and sinus tachycardia.
INHALED/NASAL STEROID
Fluticasone | ↑ fluticasone | Concomitant use of fluticasone propionate and VIRACEPT may increase plasma concentrations of fluticasone propionate. Use with caution. Consider alternatives to fluticasone propionate, particularly for long-term use.
MACROLIDE ANTIBIOTIC
Azithromycin | ↑ azithromycin | Dose adjustment of azithromycin is not recommended, but close monitoring for known side effects such as liver enzyme abnormalities and hearing impairment is warranted.
NARCOTIC ANALGESIC
Methadone | ↓ methadone | Concentrations of methadone were decreased when coadministered with VIRACEPT. Dosage of methadone may need to be increased when coadministered with VIRACEPT.
HORMONAL CONTRACEPTIVES
Ethinyl estradiol Norethindrone | ↓ ethinyl estradiol ↓ norethindrone | Concentrations of ethinyl estradiol and norethindrone were decreased when coadministered with VIRACEPT. Alternative or additional contraceptive measures should be used when oral contraceptives containing ethinyl estradiol or norethindrone and VIRACEPT are coadministered.
PDE5 INHIBITORS
Sildenafil Vardenafil Tadalafil | ↑ PDE5 Inhibitors | Concomitant use of PDE5 inhibitors and VIRACEPT should be undertaken with caution. May result in an increase in PDE5 inhibitor-associated adverse events, including hypotension, syncope, visual disturbances, and priapism. Use of PDE5 inhibitors for pulmonary arterial hypertension (PAH): • Use of sildenafil (REVATIO) is contraindicated when used for the treatment of pulmonary arterial hypertension (PAH) [see Contraindications (4)]. • The following dose adjustments are recommended for use of tadalafil (ADCIRCA™) with VIRACEPT: Coadministration of ADCIRCA in patients on VIRACEPT or coadministration of VIRACEPT in patients on ADCIRCA: Start at or adjust ADCIRCA to 20 mg once daily. Increase to 40 mg once daily based upon individual tolerability. Use of PDE5 inhibitors for erectile dysfunction: Sildenafil at a single dose not exceeding 25 mg in 48 hours, vardenafil at a single dose not exceeding 2.5 mg in 24 hours, or tadalafil at a single dose not exceeding 10 mg dose in 72 hours, is recommended. Use with increased monitoring for adverse events.
PROTON PUMP INHIBITORS
Omeprazole | ↓ nelfinavir | Omeprazole decreases the plasma concentrations of nelfinavir. Concomitant use of proton pump inhibitors and VIRACEPT may lead to a loss of virologic response and development of resistance.
ANTIPSYCHOTICS
Quetiapine | ↑ quetiapine | Initiation of VIRACEPT in patients taking quetiapine: Consider alternative antiretroviral therapy to avoid increases in quetiapine drug exposures. If coadministration is necessary, reduce the quetiapine dose to 1/6 of the current dose and monitor for quetiapine-associated adverse reactions. Refer to the quetiapine prescribing information for recommendations on adverse reaction monitoring. Initiation of quetiapine in patients taking VIRACEPT: Refer to the quetiapine prescribing information for initial dosing and titration of quetiapine.

8 USE IN SPECIFIC POPULATIONS

8.1 Pregnancy

Pregnancy Exposure Registry

There is a pregnancy exposure registry that monitors pregnancy outcomes in women exposed to VIRACEPT during pregnancy. Healthcare providers are encouraged to register patients by calling the Antiretroviral Pregnancy Registry (APR) at 1-800-258-4263.

Risk Summary

Published reports of hepatic adverse events ranging from elevated liver enzymes to hepatic failure in pregnant patients exposed to nelfinavir have been reported (see Clinical Considerations). Due to VIRACEPT's overall adverse event profile, including hepatic adverse events, and literature reports of decreased exposures in second and third trimesters, consider alternative antiretroviral drugs during pregnancy.

Available data from the APR suggests a statistically significant increase in overall risks of major birth defects with first trimester exposure with nelfinavir (3.9%) when compared with the background rate of 2.7% in one U.S. reference population (the Metropolitan Atlanta Congenital Defects Program [MACDP]), but the risk is similar to the background rate of 4.2% reported in another U.S. reference population (the Texas Birth Defects Registry [TBDR]). No pattern of defects was identified by the APR. The clinical relevance of this statistical finding is uncertain (see Data).

The estimated background risk of major birth defects and miscarriage for the indicated populations is unknown. In the U.S. general population, the estimated background risk of major birth defects and miscarriages in clinically recognized pregnancies is 2 to 4% and 15 to 20% respectively.

In animal reproductive studies, no effects on embryo-fetal development were observed when nelfinavir was administered orally to pregnant rats and rabbits during organogenesis at systemic exposures similar to or less than human exposure (based on AUC) at the maximum recommended human dose (MRHD), respectively (see Data).

Clinical Considerations

Maternal Adverse Reactions

There have been reports of hepatic adverse events ranging from elevated liver enzymes to hepatic failure in pregnant patients receiving nelfinavir as part of combination treatment of HIV-1 infection. Consider alternative antiretroviral drugs during pregnancy. If VIRACEPT is used during pregnancy, clinical monitoring is recommended [see Warnings and Precautions (5.2) and Use in Specific Populations (8.6)].

Data

Human Data

Based on prospective reports to the APR of over 1,200 live births following first trimester and over 2,700 live births following second and third trimester exposure to nelfinavir-containing regimens, there was an increase in overall rates of major birth defects (n=47) with nelfinavir when compared with the background birth defect rate of 2.7% in the U.S. reference population of the MACDP. The prevalence of birth defects in live births was 3.9% (95% CI: 2.9% to 5.1%) with first trimester exposure to nelfinavir-containing regimens and 3.1% (95% CI: 2.5% to 3.9%) with the second/third trimester exposure to nelfinavir-containing regimens. The rate for nelfinavir-containing regimens is greater than the overall rates of defects in the MACDP (2.7%) but less than rates of defects in the TBDR (4.2%). Methodological limitations of the APR include the use of MACDP as the external comparator group. Limitations of using an external comparator include differences in methodology and populations, as well as confounding due to the underlying disease; these limitations preclude an accurate comparison of outcomes. The MACDP population is not disease specific, evaluates women and infants from a limited geographic area, and does not include outcomes for births that occurred at <20 weeks gestation.

Animal Data

Nelfinavir was administered orally to pregnant rats and rabbits during organogenesis, from gestation day 6 to 17 (rats) and 7 to 20 (rabbits). There were no effects on fetal development or maternal toxicity when nelfinavir was administered to pregnant rats at systemic exposures (AUC) similar to human exposure. Administration of nelfinavir to pregnant rabbits resulted in no fetal development effects up to a dose at which a slight decrease in maternal body weight was observed; however, even at the highest dose evaluated, systemic exposure in rabbits was significantly lower than human exposure. Additional studies in rats indicated that exposure to nelfinavir in females from mid-pregnancy through lactation (gestation day 6 to lactation day 20) had no effect on the survival, growth, and development of the offspring. Subsequent reproductive performance of these offspring was also not affected by maternal exposure to nelfinavir.

8.2 Lactation

Risk Summary

The Centers for Disease Control and Prevention recommend that HIV-1 infected patients in the United States not breastfeed their infants to avoid risking potential transmission of HIV-1 infection. Based on limited published data, nelfinavir is present in low levels in human milk, and adverse effects in infants exposed to nelfinavir have been reported. Because of the potential for (1) HIV-1 transmission (in HIV-negative infants), (2) developing viral resistance (in HIV-positive infants), and (3) the potential for serious adverse reactions in breastfed infants similar to those seen in adults, instruct mothers not to breastfeed if they are receiving VIRACEPT.

8.3 Females and Males of Reproductive Potential

Contraception

Use of VIRACEPT may reduce the efficacy of estrogen-based oral contraceptives. Advise patients to use alternative or additional contraceptive measures when oral contraceptives containing ethinyl estradiol or norethindrone and VIRACEPT are coadministered [see Drug Interactions (7.3)].

8.4 Pediatric Use

The safety, tolerability, pharmacokinetic profile and efficacy of VIRACEPT were evaluated in HIV infected pediatric patients from 2 to 13 years of age in multicenter clinical trials, Study 556 and PACTG 337 [see Clinical Pharmacology (12.3) and Clinical Studies (14.3)]. In patients less than 2 years of age, VIRACEPT was found to be safe at the doses studied, but a reliably effective dose could not be established [see Dosage and Administration (2.2), Adverse Reactions (6.2), and Clinical Pharmacology (12.3)]. The pharmacokinetic profile, safety and antiviral activity of VIRACEPT in adolescent patients 13 years and older is supported by data from the adult clinical trials where some trials allowed enrolment of subjects 13 years and older. Thus, the data for adolescents and adults were analyzed collectively [see Adverse Reactions (6.1)].

8.5 Geriatric Use

Clinical studies of VIRACEPT did not include sufficient numbers of subjects aged 65 and over to determine whether they respond differently from younger subjects.

8.6 Hepatic Impairment

VIRACEPT should not be used in patients with either moderate or severe hepatic impairment (Child-Pugh B or C, score greater than or equal to 7) [see Warnings and Precautions (5.2) and Clinical Pharmacology (12.3)]. No dose adjustment of VIRACEPT is necessary for patients with mild hepatic impairment (Child-Pugh A, score 5–6).

8.7 Renal Impairment

The safety and efficacy of VIRACEPT have not been established in patients with renal impairment.

10 OVERDOSAGE

Human experience of acute overdose with VIRACEPT is limited. There is no specific antidote for overdose with VIRACEPT. If indicated, elimination of unabsorbed drug should be achieved by emesis or gastric lavage. Administration of activated charcoal may also be used to aid removal of unabsorbed drug. Since nelfinavir is highly protein bound, dialysis is unlikely to significantly remove drug from blood.

11 DESCRIPTION

VIRACEPT® (nelfinavir mesylate) is an inhibitor of the human immunodeficiency virus type 1 (HIV-1) protease. VIRACEPT Tablets are available for oral administration as a light-blue, capsule-shaped tablet with a clear film coating in 250 mg strength (as nelfinavir-free base) and as a white oval tablet with a clear film coating in 625 mg strength (as nelfinavir-free base). Each tablet contains the following common inactive ingredients: calcium silicate, crospovidone, magnesium stearate, hypromellose, and triacetin. In addition, the 250 mg tablet contains FD&C blue #2 powder and the 625 mg tablet contains colloidal silicon dioxide. VIRACEPT Oral Powder is available for oral administration in a 50 mg/g strength (as nelfinavir-free base) in bottles. The oral powder also contains the following inactive ingredients: microcrystalline cellulose, maltodextrin, dibasic potassium phosphate, crospovidone, hypromellose, aspartame, sucrose palmitate, and natural and artificial flavor. The chemical name for nelfinavir mesylate is [3S-[2(2S*, 3S*), 3α,4aβ,8aβ]]-N-(1,1-dimethylethyl)decahydro-2-[2-hydroxy-3-[(3-hydroxy-2-methylbenzoyl)amino]-4-(phenylthio)butyl]-3-isoquinoline carboxamide mono-methanesulfonate (salt) and the molecular weight is 663.90 (567.79 as the free base). Nelfinavir mesylate has the following structural formula:

Nelfinavir mesylate is a white to off-white amorphous powder, slightly soluble in water at pH ≤4 and freely soluble in methanol, ethanol, 2-propanol and propylene glycol.

12 CLINICAL PHARMACOLOGY

12.1 Mechanism of Action

Nelfinavir is an inhibitor of the HIV-1 protease [see Microbiology (12.4)].

12.2 Pharmacodynamics

Effects on Electrocardiogram

The effect of Viracept at the recommended dose of 1250 mg twice daily on the QTcF interval administered with a low fat meal (20% fat) was evaluated in a randomized, placebo and active (moxifloxacin 400 mg once daily) controlled, crossover study in 66 healthy subjects. The maximum mean time-matched (95% upper confidence bound) differences in QTcF interval from placebo after baseline-correction was below 10 milliseconds, the threshold of clinical concern. This finding was unchanged when a single supratherapeutic dose of Viracept 3125 mg was administered following a 3-day administration of Viracept 1250 mg twice daily. The exposure at 3125 mg was 1.4-fold that at 1250 mg. The dose of 3125 mg in this study did not achieve the anticipated exposures in patients taking a high fat meal (50% fat) or with concomitant administration of drugs that could increase nelfinavir exposure [see Pharmacokinetics (12.3)].

No subject in any group had an increase in QTcF of ≥60 milliseconds from baseline. No subject experienced an interval exceeding the potentially clinically relevant threshold of 500 milliseconds.

12.3 Pharmacokinetics

The pharmacokinetic properties of nelfinavir were evaluated in healthy volunteers and HIV-infected patients; no substantial differences were observed between the two groups.

Absorption

Pharmacokinetic parameters of nelfinavir (area under the plasma concentration-time curve during a 24-hour period at steady-state [AUC24], peak plasma concentrations [Cmax], morning and evening trough concentrations [Ctrough]) from a pharmacokinetic study in HIV-positive patients after multiple dosing with 1250 mg (five 250 mg tablets) twice daily (BID) for 28 days (10 patients) and 750 mg (three 250 mg tablets) three times daily (TID) for 28 days (11 patients) are summarized in Table 7.

Table 7: Summary of a Pharmacokinetic Study in HIV-positive Patients With Multiple Dosing of 1250 mg (Five 250 mg Tablets) BID for 28 Days and 750 mg (Three 250 mg Tablets) TID for 28 Days
Regimen | AUC24 mg∙h/L | Cmax mg/L | Ctrough Morning mg/L | Ctrough Afternoon or Evening mg/L
1250 mg BID | 52.8±15.7 | 4.0±0.8 | 2.2±1.3 | 0.7±0.4
750 mg TID | 43.6±17.8 | 3.0±1.6 | 1.4±0.6 | 1.0±0.5
Data are mean ± SD

The difference between morning and afternoon or evening trough concentrations for the TID and BID regimens was also observed in healthy volunteers who were dosed at precisely 8- or 12-hour intervals.

In healthy volunteers receiving a single 1250 mg dose, the 625 mg tablet was not bioequivalent to the 250 mg tablet formulation. Under fasted conditions (n=27), the AUC and Cmax were 34% and 24% higher, respectively, for the 625 mg tablets. In a relative bioavailability assessment under fed conditions (n=28), the AUC was 24% higher for the 625 mg tablet; the Cmax was comparable for both formulations. In HIV-1 infected subjects (N=21) receiving multiple doses of 1250 mg BID under fed conditions, the 625 mg formulation was bioequivalent to the 250 mg formulation based on similarity in steady state exposure (Cmax and AUC).

Table 8 shows the summary of the steady state pharmacokinetic parameters (mean ± SD) of nelfinavir after multiple dose administration of 1250 mg BID (2 × 625 mg tablets) to HIV-infected patients (N=21) for 14 days.

Table 8: Summary of the Steady State Pharmacokinetic Parameters (Mean ± SD) of Nelfinavir After Multiple Dose Administration of 1250 mg BID (2 × 625 mg Tablets) to HIV-infected Patients (N=21) for 14 Days.
Regimen | AUC12 mg∙h/L | Cmax mg/L | Cmin mg/L
1250 mg BID | 35.3 (16.4) | 4.7 (1.9) | 1.5 (1.0)
AUC12: Steady state AUC
Cmax: Maximum plasma concentration at steady state
Cmin: Minimum plasma concentration at steady state

In healthy volunteers receiving a single 750 mg dose under fed conditions, nelfinavir concentrations were similar following administration of the 250 mg tablet and oral powder.

Effect of Food on Oral Absorption

Food increases nelfinavir exposure and decreases nelfinavir pharmacokinetic variability relative to the fasted state. In one study, healthy volunteers received a single dose of 1250 mg of VIRACEPT 250 mg tablets (5 tablets) under fasted or fed conditions (three different meals). In a second study, healthy volunteers received single doses of 1250 mg VIRACEPT (5 × 250 mg tablets) under fasted or fed conditions (two different fat content meals). The results from the two studies are summarized in Table 9 and Table 10, respectively.

Table 9: Increase in AUC, Cmax and Tmax for Nelfinavir in Fed State Relative to Fasted State Following 1250 mg VIRACEPT (5 × 250 mg Tablets)
Number of Kcal | % Fat | Number of subjects | AUC fold increase | Cmax fold increase | Increase in Tmax (hr)
125 | 20 | n=21 | 2.2 | 2.0 | 1.00
500 | 20 | n=22 | 3.1 | 2.3 | 2.00
1000 | 50 | n=23 | 5.2 | 3.3 | 2.00

Table 10: Increase in Nelfinavir AUC, Cmax and Tmax in Fed Low Fat (20%) versus High Fat (50%) State Relative to Fasted State Following 1250 mg VIRACEPT (5 × 250 mg Tablets)
Number of Kcal | % Fat | Number of subjects | AUC fold increase | Cmax fold increase | Increase in Tmax (hr)
500 | 20 | n=22 | 3.1 | 2.5 | 1.8
500 | 50 | n=22 | 5.1 | 3.8 | 2.1

Nelfinavir exposure can be increased by increasing the calorie or fat content in meals taken with VIRACEPT.

A food effect study has not been conducted with the 625 mg tablet. However, based on a cross-study comparison (n=26 fed vs. n=26 fasted) following single dose administration of nelfinavir 1250 mg, the magnitude of the food effect for the 625 mg nelfinavir tablet appears comparable to that of the 250 mg tablets. VIRACEPT should be taken with a meal.

Distribution

The apparent volume of distribution following oral administration of nelfinavir was 2–7 L/kg. Nelfinavir in serum is extensively protein-bound (>98%).

Metabolism

Unchanged nelfinavir comprised 82–86% of the total plasma radioactivity after a single oral 750 mg dose of ^14C-nelfinavir. In vitro, multiple cytochrome P-450 enzymes including CYP3A and CYP2C19 are responsible for metabolism of nelfinavir. One major and several minor oxidative metabolites were found in plasma. The major oxidative metabolite has in vitro antiviral activity comparable to the parent drug.

Elimination

The terminal half-life in plasma was typically 3.5 to 5 hours. The majority (87%) of an oral 750 mg dose containing ^14C-nelfinavir was recovered in the feces; fecal radioactivity consisted of numerous oxidative metabolites (78%) and unchanged nelfinavir (22%). Only 1–2% of the dose was recovered in urine, of which unchanged nelfinavir was the major component.

Specific Populations

Hepatic Impairment

The steady-state pharmacokinetics of nelfinavir (1250 mg BID for 2 weeks) was studied in HIV-seronegative subjects with mild (Child-Pugh Class A; n=6) or moderate (Child-Pugh Class B; n=6) hepatic impairment. When compared with subjects with normal hepatic function, the Cmax and AUC of nelfinavir were not significantly different in subjects with mild hepatic impairment but were increased by 22% and 62%, respectively, in subjects with moderate hepatic impairment. The steady-state pharmacokinetics of nelfinavir has not been studied in HIV-seronegative subjects with severe hepatic impairment.

The steady-state pharmacokinetics of nelfinavir has not been studied in HIV-positive patients with any degree of hepatic impairment.

Renal Impairment

The pharmacokinetics of nelfinavir have not been studied in patients with renal impairment.

Gender and Race

No significant pharmacokinetic differences have been detected between males and females. Pharmacokinetic differences due to race have not been evaluated.

Pediatrics

The pharmacokinetics of nelfinavir have been investigated in 5 studies in pediatric patients from birth to 13 years of age either receiving VIRACEPT three times or twice daily. The dosing regimens and associated AUC24 values are summarized in Table 11.

Table 11: Summary of Steady-state AUC24 of Nelfinavir in Pediatric Studies
Protocol number | Dosing regimen [Protocol specified dose (actual dose range)] | N [N: number of subjects with evaluable pharmacokinetic results] | Age | AUC24 (mg∙hr/L) arithmetic mean ± SD
AG1343-524 | 20 (19–28) mg/kg TID | 14 | 2–13 years | 56.1±29.8
PACTG-725 | 55 (48–60) mg/kg BID | 6 | 3–11 years | 101.8±56.1
PENTA 7 | 40 (34–43) mg/kg TID | 4 | 2–9 months | 33.8±8.9
PENTA 7 | 75 (55–83) mg/kg BID | 12 | 2–9 months | 37.2±19.2
PACTG-353 | 40 (14–56) mg/kg BID | 10 | 6 weeks | 44.1±27.4
PACTG-353 | 40 (14–56) mg/kg BID | 10 | 1 week | 45.8±32.1
Ctrough values are not presented in the table because they are not available for all studies

Pharmacokinetic data are also available for 86 patients (age 2 to 12 years) who received VIRACEPT 25–35 mg/kg TID in Study AG1343-556. The pharmacokinetic data from Study AG1343-556 were more variable than data from other studies conducted in the pediatric population; the 95% confidence interval for AUC24 was 9 to 121 mg∙hr/L.

Overall, use of VIRACEPT in the pediatric population is associated with highly variable drug exposure. The high variability may be due to inconsistent food intake in pediatric patients [see Dosage and Administration (2.2)].

Geriatric Patients

The pharmacokinetics of nelfinavir have not been studied in patients over 65 years of age.

Drug Interactions

CYP3A and CYP2C19 appear to be the predominant enzymes that metabolize nelfinavir in humans. The potential ability of nelfinavir to inhibit the major human cytochrome P450 enzymes (CYP3A, CYP2C19, CYP2D6, CYP2C9, CYP1A2 and CYP2E1) has been investigated in vitro. Only CYP3A was inhibited at concentrations in the therapeutic range. Specific drug interaction studies were performed with nelfinavir and a number of drugs. Table 12 summarizes the effects of nelfinavir on the geometric mean AUC, Cmax and Cmin of coadministered drugs. Table 13 shows the effects of coadministered drugs on the geometric mean AUC, Cmax and Cmin of nelfinavir.

Table 12: Drug Interactions: Changes in Pharmacokinetic Parameters for Coadministered Drug in the Presence of VIRACEPT
 |  |  | % Change of Coadministered Drug Pharmacokinetic Parameters [↑ Indicates increase; ↓ Indicates decrease; ↔ Indicates no change (geometric mean exposure increased, or decreased <10%)] (90% CI)
Coadministered Drug | Nelfinavir Dose | N | AUC | Cmax | Cmin
HIV-Protease Inhibitors
Indinavir 800 mg Single Dose | 750 mg q8h × 7 days | 6 | ↑51% (↑29–↑77%) | ↓10% (↓28–↑13%) | NA
Ritonavir 500 mg Single Dose | 750 mg q8h × 5 doses | 10 | ↔ | ↔ | NA
Saquinavir 1200 mg Single Dose [Using the soft-gelatin capsule formulation of saquinavir 1200 mg] | 750 mg TID × 4 days | 14 | ↑392% (↑291–↑521%) | ↑179% (↑117–↑259%) | NA
Amprenavir 800 mg TID × 14 days | 750 mg TID × 14 days | 6 | ↔ | ↓14% (↓38–↑20%) | ↑189% (↑52–↑448%)
Nucleoside Reverse Transcriptase Inhibitors
Lamivudine 150 mg Single Dose | 750 mg q8h × 7–10 days | 11 | ↑10% (↑2–↑18%) | ↑31% (↑9–↑56%) | NA
Zidovudine 200 mg Single Dose | 750 mg q8h × 7–10 days | 11 | ↓35% (↓29–↓40%) | ↓31% (↓13–↓46%) | NA
Non-nucleoside Reverse Transcriptase Inhibitors
Efavirenz 600 mg qd × 7 days | 750 mg q8h × 7 days | 10 | ↓12% (↓31–↑12%) | ↓12% (↓29–↑8%) | ↓22% (↓54–↑32%)
Delavirdine 400 mg q8h × 14 days | 750 mg q8h × 7 days | 7 | ↓31% (↓57–↑10%) | ↓27% (↓49–↑4%) | ↓33% (↓70–↑49%)
Anti-infective Agents
Rifabutin 150 mg qd × 8 days [Rifabutin 150 mg qd changes are relative to Rifabutin 300 mg qd × 8 days without coadministration with nelfinavir] | 750 mg q8h × 7–8 days [Comparable changes in rifabutin concentrations were observed with VIRACEPT 1250 mg q12h × 7 days] | 12 | ↑83% (↑72–↑96%) | ↑19% (↑11–↑28%) | ↑177% (↑144–↑215%)
Rifabutin 300 mg qd × 8 days | 750 mg q8h × 7–8 days | 10 | ↑207% (↑161–↑263%) | ↑146% (↑118–↑178%) | ↑305% (↑245–↑375%)
Azithromycin 1200 mg Single Dose | 750 mg TID × 11 days | 12 | ↑112% (↑80–↑150%) | ↑136% (↑77–↑215%) | NA
HMG-CoA Reductase Inhibitors
Atorvastatin 10 mg qd × 28 days | 1250 mg BID × 14 days | 15 | ↑74% (↑41–↑116%) | ↑122% (↑68–↑193%) | ↑39% (↓21–↑145%)
Simvastatin 20 mg qd × 28 days | 1250 mg BID × 14 days | 16 | ↑505% (↑393–↑643%) | ↑517% (↑367–↑715%) | ND
Other Agents
Ethinyl estradiol 35 µg qd × 15 days | 750 mg q8h × 7 days | 12 | ↓47% (↓42–↓52%) | ↓28% (↓16–↓37%) | ↓62% (↓57–↓67%)
Norethindrone 0.4 mg qd × 15 days | 750 mg q8h × 7 days | 12 | ↓18% (↓13–↓23%) | ↔ | ↓46% (↓38–↓53%)
Methadone 80 mg ± 21 mg qd [Changes are reported for total plasma methadone; changes for the individual R-enantiomer and S-enantiomer were similar] >1 month | 1250 mg BID × 8 days | 13 | ↓47% (↓42–↓51%) | ↓46% (↓42–↓49%) | ↓53% (↓49–↓57%)
Phenytoin 300 mg qd × 14 days [Phenytoin exposure measures are reported for total phenytoin exposure. The effect of nelfinavir on unbound phenytoin was similar] | 1250 mg BID × 7 days | 12 | ↓29% (↓17–↓39%) | ↓21% (↓12–↓29%) | ↓39% (↓27–↓49%)
NA: Not relevant for single-dose treatment; ND: Cannot be determined

Table 13: Drug Interactions: Changes in Pharmacokinetic Parameters for Nelfinavir in the Presence of the Coadministered Drug
 |  |  | % Change of Nelfinavir Pharmacokinetic Parameters [↑ Indicates increase; ↓ Indicates decrease; ↔ Indicates no change (geometric mean exposure increased or decreased <10%)] (90% CI)
Coadministered Drug | Nelfinavir Dose | N | AUC | Cmax | Cmin
HIV-Protease Inhibitors
Indinavir 800 mg q8h × 7 days | 750 mg Single Dose | 6 | ↑83% (↑42–↑137%) | ↑31% (↑16–↑48%) | NA
Ritonavir 500 mg q12h × 3 doses | 750 mg Single Dose | 10 | ↑152% (↑96–↑224%) | ↑44% (↑28–↑63%) | NA
Saquinavir 1200 mg TID × 4 days [Using the soft-gelatin capsule formulation of saquinavir 1200 mg] | 750 mg Single Dose | 14 | ↑18% (↑7–↑30%) | ↔ | NA
Nucleoside Reverse Transcriptase Inhibitors
Didanosine 200 mg Single Dose | 750 mg Single Dose | 9 | ↔ | ↔ | NA
Zidovudine 200 mg + Lamivudine 150 mg Single Dose | 750 mg q8h × 7–10 days | 11 | ↔ | ↔ | ↔
Non-nucleoside Reverse Transcriptase Inhibitors
Efavirenz 600 mg qd × 7 days | 750 mg q8h × 7 days | 7 | ↑20% (↑8–↑34%) | ↑21% (↑10–↑33%) | ↔
Nevirapine 200 mg qd × 14 days followed by 200 mg BID × 14 days | 750 mg TID × 36 days | 23 | ↔ | ↔ | ↓32% (↓50–↑5%)
Delavirdine 400 mg q8h × 7 days | 750 mg q8h × 14 days | 12 | ↑107% (↑83–↑135%) | ↑88% (↑66–↑113%) | ↑136% (↑103–↑175%)
Anti-infective Agents
Ketoconazole 400 mg qd × 7 days | 500 mg q8h × 5–6 days | 12 | ↑35% (↑24–↑46%) | ↑25% (↑11–↑40%) | ↑14% (↓23–↑69%)
Rifabutin 150 mg qd × 8 days | 750 mg q8h × 7–8 days | 11 | ↓23% (↓14–↓31%) | ↓18% (↓8–↓27%) | ↓25% (↓8–↓39%)
 | 1250 mg q12h × 7–8 days | 11 | ↔ | ↔ | ↓15% (↓43–↑27%)
Rifabutin 300 mg qd × 8 days | 750 mg q8h × 7–8 days | 10 | ↓32% (↓15–↓46%) | ↓24% (↓10–↓36%) | ↓53% (↓15–↓73%)
Rifampin 600 mg qd × 7 days | 750 mg q8h × 5–6 days | 12 | ↓83% (↓79–↓86%) | ↓76% (↓69–↓82%) | ↓92% (↓86–↓95%)
Azithromycin 1200 mg Single Dose | 750 mg tid × 9 days | 12 | ↓15% (↓7–↓22%) | ↓10% (↓19–↑1%) | ↓29% (↓19–↓38%)
Other Agents
Phenytoin 300 mg qd × 7 days | 1250 mg BID × 14 days | 15 | ↔ | ↔ | ↓18% (↓45–↑23%)
Omeprazole 40 mg qd × 4 days administered 30 minutes before nelfinavir | 1250 mg BID × 4 days | 19 | ↓36% (↓20–↓49%) | ↓37% (↓23–↓49%) | ↓39% (↓15–↓57%)
NA: Not relevant for single-dose treatment

12.4 Microbiology

Mechanism of Action

Nelfinavir is an inhibitor of the HIV-1 protease. Inhibition of the viral protease prevents cleavage of the gag and gag-pol polyprotein resulting in the production of immature, non-infectious virus.

Antiviral Activity in Cell Culture

The antiviral activity of nelfinavir has been demonstrated in both acute and/or chronic HIV infections in lymphoblastoid cell lines, peripheral blood lymphocytes, and monocytes/macrophages. Nelfinavir was found to be active against several laboratory strains and clinical isolates of HIV-1, and the HIV-2 strain ROD. The EC95 (95% effective concentration) of nelfinavir ranged from 7 to 196 nM. Drug combination studies with other HIV-1 protease inhibitors showed nelfinavir had antagonistic interactions with indinavir, additive interactions with ritonavir or saquinavir, and synergistic interactions with amprenavir and lopinavir. Minimal to no cellular cytotoxicity was observed with any of these protease inhibitors alone or in combination with nelfinavir. In combination with reverse transcriptase inhibitors, nelfinavir demonstrated additive (didanosine or stavudine) to synergistic (abacavir, delavirdine, efavirenz, emtricitabine, lamivudine, nevirapine, tenofovir, zalcitabine, or zidovudine) antiviral activity without enhanced cytotoxicity. Nelfinavir's anti-HIV activity was not antagonized by the anti-HCV drug ribavirin.

Resistance

HIV-1 isolates with reduced susceptibility to nelfinavir have been selected in cell culture. HIV-1 isolates from selected patients treated with nelfinavir alone or in combination with reverse transcriptase inhibitors were monitored for phenotypic (n=19) and genotypic (n=195, 157 of which were evaluable) changes in clinical trials over a period of 2 to 82 weeks. One or more viral protease mutations at amino acid positions 30, 35, 36, 46, 71, 77, and 88 were detected in the HIV-1 of >10% of patients with evaluable isolates. The overall incidence of the D30N substitution in the viral protease of evaluable isolates (n=157) from patients receiving nelfinavir monotherapy or nelfinavir in combination with zidovudine and lamivudine or stavudine was 54.8%. The overall incidence of other substitutions associated with primary protease inhibitor resistance was 9.6% for the L90M substitution, whereas substitutions at 48, 82, or 84 were not observed. Of the 19 clinical isolates for which both phenotypic and genotypic analyses were performed, 9 showed reduced susceptibility (5- to 93-fold) to nelfinavir in cell culture. All 9 isolates possessed one or more mutations in the viral protease gene. Amino acid position 30 appeared to be the most frequent mutation site.

Cross-resistance

Non-clinical Studies: Patient-derived recombinant HIV-1 isolates containing the D30N substitution (n=4) and demonstrating high-level (>10-fold) nelfinavir-resistance remained susceptible (<2.5-fold resistance) to amprenavir, indinavir, lopinavir, and saquinavir in cell culture. Patient-derived recombinant HIV-1 isolates containing the L90M substitution (n=8) demonstrated moderate to high-level resistance to nelfinavir and had varying levels of susceptibility to amprenavir, indinavir, lopinavir, and saquinavir in cell culture. Most patient-derived recombinant isolates with phenotypic and genotypic evidence of reduced susceptibility (>2.5-fold) to amprenavir, indinavir, lopinavir, and/or saquinavir demonstrated high-level cross-resistance to nelfinavir. Amino acid substitutions associated with resistance to other protease inhibitors (e.g., G48V, V82A/F/T, I84V, L90M) appeared to confer high-level cross-resistance to nelfinavir. Following ritonavir therapy 6 of 7 clinical isolates with decreased ritonavir susceptibility (8- to 113-fold) compared to baseline also exhibited decreased susceptibility to nelfinavir (5- to 40-fold). Cross-resistance between nelfinavir and reverse transcriptase inhibitors is unlikely because different enzyme targets are involved. Clinical isolates (n=5) with decreased susceptibility to lamivudine, nevirapine, or zidovudine remain fully susceptible to nelfinavir.

Clinical Studies: There have been no controlled or comparative studies evaluating the virologic response to subsequent protease inhibitor-containing regimens in subjects who have demonstrated loss of virologic response to a nelfinavir-containing regimen. However, virologic response was evaluated in a single-arm prospective study of 26 subjects with extensive prior antiretroviral experience with reverse transcriptase inhibitors (mean 2.9) who had received nelfinavir for a mean duration of 59.7 weeks and were switched to a ritonavir (400 mg BID)/saquinavir hard-gel (400 mg BID)-containing regimen after a prolonged period of nelfinavir failure (median 48 weeks). Sequence analysis of HIV-1 isolates prior to switch demonstrated a D30N or an L90M substitution in 18 and 6 subjects, respectively. Subjects remained on therapy for a mean of 48 weeks (range 40 to 56 weeks) where 17 (65%) and 13 (50%) of the 26 subjects were treatment responders with HIV-1 RNA below the assay limit of detection (<500 HIV-1 RNA copies/mL, Chiron bDNA) at 24 and 48 weeks, respectively.

13 NONCLINICAL TOXICOLOGY

13.1 Carcinogenesis, Mutagenesis, Impairment of Fertility

Carcinogenicity studies in mice and rats were conducted with nelfinavir at oral doses up to 1000 mg/kg/day. No evidence of a tumorigenic effect was noted in mice at systemic exposures (Cmax) up to 9-fold those measured in humans at the recommended therapeutic dose (750 mg TID or 1250 mg BID). In rats, thyroid follicular cell adenomas and carcinomas were increased in males at 300 mg/kg/day and higher and in females at 1000 mg/kg/day. Systemic exposures (Cmax) at 300 and 1000 mg/kg/day were 1- to 3-fold, respectively, those measured in humans at the recommended therapeutic dose. Repeated administration of nelfinavir to rats produced effects consistent with hepatic microsomal enzyme induction and increased thyroid hormone deposition; these effects predispose rats, but not humans, to thyroid follicular cell neoplasms. Nelfinavir showed no evidence of mutagenic or clastogenic activity in a battery of in vitro and in vivo genetic toxicology assays. These studies included bacterial mutation assays in S. typhimurium and E. coli, a mouse lymphoma tyrosine kinase assay, a chromosomal aberration assay in human lymphocytes, and an in vivo mouse bone marrow micronucleus assay.

Nelfinavir produced no effects on either male or female mating and fertility or embryo survival in rats at systemic exposures comparable to the human therapeutic exposure.

14 CLINICAL STUDIES

Description of Clinical Studies

The efficacy of VIRACEPT is based on analyses of multiple clinical studies in HIV-1 infected antiretroviral treatment-naïve and experienced adult patients. In the adult clinical studies described below, efficacy was evaluated by the percent of patients with plasma HIV RNA <400 copies/mL (Studies 511 and 542), <500 copies/mL (Study ACTG 364), or <50 copies/mL (Study Avanti 3). In the analysis presented in each figure, patients who terminated the study early for any reason, switched therapy due to inadequate efficacy or who had a missing HIV-RNA measurement that was either preceded or followed by a measurement above the limit of assay quantification were considered to have HIV-RNA above 400 copies/mL, above 500 copies/mL, or above 50 copies/mL at subsequent time points, depending on the study's definition of virologic failure.

14.1 Studies in Antiretroviral Treatment Naïve Adult Patients

Study 511: VIRACEPT + zidovudine + lamivudine versus zidovudine + lamivudine

Study 511 is a double-blind, randomized, placebo-controlled trial comparing treatment with zidovudine (ZDV; 200 mg TID) and lamivudine (3TC; 150 mg BID) plus 2 doses of VIRACEPT (750 mg and 500 mg TID) to zidovudine (200 mg TID) and lamivudine (150 mg BID) alone in 297 antiretroviral naïve HIV-1 infected patients. The median age was 35 years [range 21 to 63]; 89% were male and 78% were Caucasian. Mean baseline CD4 cell count was 288 cells/mm^3 and mean baseline plasma HIV RNA was 5.21 log10 copies/mL (160,394 copies/mL). The proportion of patients with plasma HIV RNA <400 copies/mL at Week 48 was 86%, as summarized in Figure 1. The mean change in CD4 cell count at Week 48 was 207.6 cells/mm^3.

Figure 1
Study 511: Percentage of Patients With HIV RNA Below 400 Copies/mL

Study 542: VIRACEPT BID + stavudine + lamivudine compared to VIRACEPT TID + stavudine + lamivudine

Study 542 is a, randomized, open-label trial comparing the HIV RNA suppression achieved by VIRACEPT 1250 mg BID versus VIRACEPT 750 mg TID in patients also receiving stavudine (d4T; 30–40 mg BID) and lamivudine (3TC; 150 mg BID). Patients had a median age of 36 years (range 18 to 83), were 84% male, and were 91% Caucasian. Patients had received less than 6 months of therapy with nucleoside transcriptase inhibitors and were naïve to protease inhibitors. Mean baseline CD4 cell count was 296 cells/mm^3 and mean baseline plasma HIV RNA was 5.0 log10 copies/mL (100,706 copies/mL).

Results showed that there was no significant difference in mean CD4 cell count among treatment groups; the mean increases from baseline for the BID and TID arms were 150 cells/mm^3 at 24 weeks and approximately 200 cells/mm^3 at 48 weeks.

The percent of patients with HIV RNA <400 copies/mL and the outcomes of patients through 48 weeks of treatment are summarized in Table 14.

Table 14: Outcomes of Randomized Treatment Through 48 Weeks
Outcome | VIRACEPT 1250 mg BID Regimen | VIRACEPT 750 mg TID Regimen
Number of patients evaluable [Twelve patients in the BID arm and fourteen patients in the TID arm had not yet reached 48 weeks of therapy.] | 323 | 192
HIV-1 RNA <400 copies/mL | 198 (61%) | 111 (58%)
HIV-1 RNA ≥400 copies/mL | 46 (14%) | 22 (11%)
Discontinued due to VIRACEPT toxicity [These rates only reflect dose-limiting toxicities that were counted as the initial reason for treatment failure in the analysis [see Adverse Reactions (6)].] | 9 (3%) | 2 (1%)
Discontinued due to other antiretroviral agents' toxicity | 3 (1%) | 3 (2%)
Others [Consent withdrawn, lost to follow-up, intercurrent illness, noncompliance or missing data; all assumed as failures.] | 67 (21%) | 54 (28%)

Study Avanti 3: VIRACEPT TID + zidovudine + lamivudine compared to zidovudine + lamivudine

Study Avanti 3 was a placebo-controlled, randomized, double-blind study designed to evaluate the safety and efficacy of VIRACEPT (750 mg TID) in combination with zidovudine (ZDV; 300 mg BID) and lamivudine (3TC; 150 mg BID) (n=53) versus placebo in combination with ZDV and 3TC (n=52) administered to antiretroviral-naïve patients with HIV infection and a CD4 cell count between 150 and 500 cells/μL. Patients had a mean age of 35 (range 22–59), were 89% male, and 88% Caucasian. Mean baseline CD4 cell count was 304 cells/mm^3 and mean baseline plasma HIV RNA was 4.8 log10 copies/mL (57,887 copies/mL). The percent of patients with plasma HIV RNA <50 copies/mL at 52 weeks was 54% for the (VIRACEPT + ZDV + 3TC)-treatment group and 13% for the (ZDV + 3TC)-treatment group.

14.2 Studies in Antiretroviral Treatment Experienced Adult Patients

Study ACTG 364: VIRACEPT TID + 2NRTIs compared to efavirenz + 2NRTIs compared to VIRACEPT + efavirenz + 2NRTIs

Study ACTG 364 was a randomized, double-blind study that evaluated the combination of VIRACEPT 750 mg TID and/or efavirenz 600 mg QD with 2 NRTIs (either didanosine [ddI] + d4T, ddI + 3TC, or d4T + 3TC) in patients with prolonged prior nucleoside exposure who had completed 2 previous ACTG studies. Patients had a mean age of 41 years (range 18 to 75), were 88% male, and were 74% Caucasian. Mean baseline CD4 cell count was 389 cells/mm^3 and mean baseline plasma HIV RNA was 3.9 log10 copies/mL (7,954 copies/mL).

The percent of patients with plasma HIV RNA <500 copies/mL at 48 weeks was 42%, 62%, and 72% for the VIRACEPT (n=66), EFV (n=65), and VIRACEPT + EFV (n=64) treatment groups, respectively.

14.3 Studies in Pediatric Patients

The pharmacokinetic profile, safety and antiviral activity of VIRACEPT in pediatric patients 2 years of age up to 13 years were evaluated in 2 randomized studies.

Study 556 was a randomized, double-blind, placebo-controlled trial with VIRACEPT or placebo coadministered with ZDV and ddI in 141 HIV-positive children who had received minimal antiretroviral therapy. The mean age of the children was 3.9 years. Ninety four (67%) children were between 2–12 years, and 47 (33%) were < 2 years of age. The mean baseline HIV RNA value was 5.0 log for all patients and the mean CD4 cell count was 886 cells/mm^3 for all patients. The efficacy of VIRACEPT measured by HIV RNA <400 at 48 weeks in children ≥2 years of age was 26% compared to 2% of placebo patients (p=0.0008). In the children < 2 years of age, only 1 of 27 and 2 of 20 maintained an undetectable HIV RNA level at 48 weeks for placebo and VIRACEPT patients, respectively.

PACTG 377 was an open-label study that randomized 181 HIV treatment-experienced pediatric patients to receive: d4T+NVP+RTV, d4T+3TC+NFV, or d4T+3TC+NVP+NFV with NFV given on a TID schedule. The median age was 5.9 years and 46% were male. At baseline the median HIV RNA was 4.4 log and median CD4 cell count was 690 cells/mm^3. Substudy PACTG 725 evaluated d4T+3TC+NFV with NFV given on a BID schedule. The proportion of patients with detectable viral load at baseline achieving HIV RNA <400 copies/mL at 48 weeks was: 41% for d4T+NVP+RTV, 42% for d4T+3TC+NFV, 30% for d4T+NVP+NFV, and 52% for d4T+3TC+NVP+NFV. No significant clinical differences were identified between patients receiving VIRACEPT in BID or TID schedules.

VIRACEPT has been evaluated in 2 studies of young infants. The PENTA 7 study was an open-label study to evaluate the toxicity, tolerability, pharmacokinetics, and activity of NFV+d4T+ddI in 20 HIV-infected infants less than 12 weeks of age. PACTG 353 evaluated the pharmacokinetics and safety of VIRACEPT in infants born to HIV-infected women receiving NFV as part of combination therapy during pregnancy.

The following issues should be considered when initiating VIRACEPT in pediatric patients:

- In pediatric patients ≥2 years of age receiving VIRACEPT as part of triple combination antiretroviral therapy in randomized studies, the proportion of patients achieving a HIV RNA level <400 copies/mL through 48 weeks ranged from 26% to 42%.
- Response rates in children <2 years of age appeared to be poorer than those in patients ≥2 years of age in some studies.
- Highly variable drug exposure remains a significant problem in the use of VIRACEPT in pediatric patients. Unpredictable drug exposure may be exacerbated in pediatric patients because of increased clearance compared to adults and difficulties with compliance and adequate food intake with dosing. Pharmacokinetic results from the pediatric studies are reported in Table 11 [see Clinical Pharmacology (12.3)].

The pharmacokinetic profile, safety and antiviral activity of VIRACEPT in adolescent patients 13 years and older is supported by data from the adult clinical trials where some trials allowed enrolment of subjects 13 years and older. Thus, the data for adolescents and adults were analyzed collectively.

16 HOW SUPPLIED/STORAGE AND HANDLING

VIRACEPT (nelfinavir mesylate) 250 mg: Light-blue, capsule-shaped tablets with a clear film coating engraved with "VIRACEPT" on one side and "250 mg" on the other.

Bottles of 300 (250 mg) tablets – NDC 63010-010-30

VIRACEPT (nelfinavir mesylate) 625 mg: White oval tablet with a clear film coating engraved with "V" on one side and "625" on the other.

Bottles of 120 (625 mg) tablets – NDC 63010-027-70

VIRACEPT (nelfinavir mesylate) Oral Powder is available as a 50 mg/g off-white powder containing 50 mg (as nelfinavir free base) in each level scoopful (1 gram).

Multiple use bottles of 144 grams of powder with scoop …….NDC 63010-011-90

STORAGE AND HANDLING

VIRACEPT tablets and oral powder should be stored at 15° to 30°C (59° to 86°F).

Keep container tightly closed. Dispense in original container.

17 PATIENT COUNSELING INFORMATION

See FDA-approved patient labeling (Patient Information)

A statement to patients and healthcare providers is included on the product's bottle label: ALERT: Find out about medicines that should NOT be taken with VIRACEPT.

Instruction for Use

For optimal absorption, patients should be advised to take VIRACEPT with food.

Patients should be informed that VIRACEPT Tablets are film-coated and that this film-coating is intended to make the tablets easier to swallow.

If a dose of VIRACEPT is missed, patients should take the dose as soon as possible and then return to their normal schedule. However, if a dose is skipped, the patient should not double the next dose.

Adult or pediatric patients unable to swallow the tablets may dissolve the tablets in a small amount of water:

- Place VIRACEPT tablet(s) in small amount of water
- Once dissolved, mix the cloudy liquid well, and consume it immediately.
- The glass should be rinsed with water and the rinse swallowed to ensure the entire dose is consumed

Pediatric patients unable to swallow tablets can also use the powder formulation:

- Mix VIRACEPT Oral Powder with a small amount of water, milk, formula, soy formula, soy milk, or dietary supplements
- Once mixed, the entire contents must be consumed in order to obtain the full dose.
- If the mixture is not consumed immediately, it must be stored under refrigeration, but storage must not exceed 6 hours.
- Acidic food or juice (e.g., orange juice, apple juice, or apple sauce) are not recommended for mixing VIRACEPT Oral Powder because the combination may result in a bitter taste.
- VIRACEPT Oral Powder should not be reconstituted with water in its original container.

Drug Interactions

VIRACEPT may interact with some drugs; therefore, advise patients to report to their healthcare provider the use of any other prescription, non-prescription medication or herbal products, including St. John's wort [see Contraindications (4), Drug Interactions (7.3), and Use in Specific Populations (8.3)].

Hepatic Impairment

Patients should be informed that VIRACEPT should not be used if there is moderate or severe hepatic impairment.

Phenylketonuria

Physicians should alert patients with phenylketonuria that VIRACEPT Oral Powder contains phenylalanine

Fat Redistribution

Patients should be informed that redistribution or accumulation of body fat may occur in patients receiving antiretroviral therapy, including PREZISTA/ritonavir, and that the cause and long-term health effects of these conditions are not known at this time

The most frequent adverse event associated with VIRACEPT is diarrhea, which can usually be controlled with non-prescription drugs, such as loperamide, which slow gastrointestinal motility.

Pregnancy Registry

Advise patients that there is a pregnancy exposure registry that monitors pregnancy outcomes in women exposed to VIRACEPT during pregnancy [see Use in Specific Populations (8.1)].

Lactation

Instruct patients with HIV-1 infection not to breastfeed because HIV-1 can be passed to the infant in the breast milk [see Use in Specific Populations (8.2)].

Females and Males of Reproductive Potential

Advise females of reproductive potential that VIRACEPT may reduce the effectiveness of estrogen-based contraceptives, and to use alternative non-hormonal contraception [see Drug Interactions (7.3), Use in Specific Populations (8.3)].

VIRACEPT is a registered trademark of Agouron Pharmaceuticals, LLC

REVATIO is a registered trademark of Pfizer, Inc.

ADCIRCA is a trademark of Eli Lilly and Company

This product's labeling may have been updated. For the most recent prescribing information, please visit www.pfizer.com.

LAB-0174-29.0

PATIENT INFORMATION

VIRACEPT (VI-ra-cept)
(nelfinavir mesylate)
Tablets

VIRACEPT (VI-ra-cept)
(nelfinavir mesylate)
Oral Powder

Important: VIRACEPT can interact with other medicines and cause serious side effects. It is important to know the medicines that should not be taken with VIRACEPT. See the section "Do not take VIRACEPT if you:"

What is VIRACEPT?

VIRACEPT is a prescription HIV-1 medicine used with other HIV-1 medicines to treat human immunodeficiency virus (HIV-1) infection. HIV-1 is the virus that causes Acquired Immune Deficiency Syndrome (AIDS).

It is not known if VIRACEPT is safe and effective in children less than 2 years of age.

Do not take VIRACEPT if you:

- are taking any of the following medicines. VIRACEPT may cause serious life-threatening side effects or death when used with these medicines:
  - alfuzosin
  - amiodarone
  - cisapride
  - ergot-containing medicines:
    - dihydroergotamine
    - ergotamine
    - methylergonovine
  - lovastatin
  - lurasidone
  - midazolam, when taken by mouth for sedation
  - pimozide
  - quinidine
  - rifampin
  - sildenafil (Revatio®), when used for the treatment of pulmonary arterial hypertension (PAH)
  - simvastatin
  - St. John's wort (Hypericum perforatum)
  - triazolam

Before taking VIRACEPT, tell your healthcare provider about all of your medical conditions, including if you:

- have liver problems
- have kidney problems
- have phenylketonuria. VIRACEPT Oral Powder contains aspartame.
- have high blood sugar (diabetes)
- have hemophilia
- are pregnant or plan to become pregnant. VIRACEPT may harm your unborn baby.
  - Tell your healthcare provider right away if you become pregnant during treatment with VIRACEPT.
  - Hormonal forms of birth control, such as injections, vaginal rings or implants, contraceptive patches, and some birth control pills may not work during treatment with VIRACEPT. Talk to your healthcare provider about forms of birth control that may be used during treatment with VIRACEPT.
  - Pregnancy Registry. There is a pregnancy registry for women who take VIRACEPT during pregnancy. The purpose of the registry is to collect information about the health of you and your baby. Talk to your healthcare provider about how you can take part in this registry.
- are breastfeeding or plan to breastfeed. Do not breastfeed if you take VIRACEPT.
  - You should not breastfeed if you have HIV-1 because of the risk of passing HIV-1 to your baby.
  - VIRACEPT can pass into your breast milk.
  - Talk to your healthcare provider about the best way to feed your baby.

Tell your healthcare provider about all the medicines you take, including prescription and over-the-counter medicines, vitamins and herbal supplements. Some medicines interact with VIRACEPT. Keep a list of your medicines to show your healthcare provider and pharmacist.

- You can ask your healthcare provider or pharmacist for a list of medicines that interact with VIRACEPT.
- Do not start taking a new medicine without telling your healthcare provider. Your healthcare provider can tell you if it is safe to take VIRACEPT with other medicines.
  - Especially tell your healthcare provider if you take medicines that contain didanosine. Take VIRACEPT with food one hour after or more than two hours before you take didanosine.

How should I take VIRACEPT?

- You should stay under a healthcare provider's care during treatment with VIRACEPT.
- Take VIRACEPT every day exactly as prescribed by your healthcare provider.
- Do not change your dose of VIRACEPT or stop treatment without talking to your healthcare provider first.
- Take VIRACEPT with a meal.
- VIRACEPT is usually taken 2 or 3 times each day. Your healthcare provider will tell you how much VIRACEPT to take and when to take it.
- If your child is taking VIRACEPT, your child's healthcare provider will decide the right dose based on your child's weight.
- VIRACEPT Tablets are film-coated to help make the tablets easier to swallow.
- If you or your child are unable to swallow the tablets:
  - You may dissolve the tablets in a small amount of water. Once the tablets are dissolved, the liquid will be cloudy.
  - Mix the cloudy liquid well, and then drink it right away.
  - Rinse the glass with water and drink the water to ensure that you take the full dose of VIRACEPT.
- If you miss a dose of VIRACEPT, take it as soon as possible. If you skip a dose, do not double the next dose.
- If you take too much VIRACEPT, call your healthcare provider or go to the nearest hospital emergency room right away.
- Do not run out of VIRACEPT. Get your VIRACEPT refilled from your healthcare provider or pharmacy before you run out.

How should VIRACEPT Oral Powder be prepared?

- Your healthcare provider should tell you how much VIRACEPT Oral Powder to use.
- VIRACEPT Oral Powder comes with a scoop for measuring. Ask your healthcare provider or pharmacist for help measuring the correct amount of VIRACEPT Oral Powder.
- Do not mix VIRACEPT Oral Powder in the container that it comes in. Measure the correct amount of VIRACEPT Oral Powder into a cup.
- You may mix VIRACEPT Oral Powder with a small amount of water, milk, formula, soy formula, soy milk, or liquid dietary supplements.
- You should not mix VIRACEPT Oral Powder with acidic food or juice, such as orange juice, apple juice, or applesauce because the mixture may taste bitter.
- Your child should drink all of the mixture to be sure that the entire dose of VIRACEPT is taken.
- If your child does not take the dose right away, store in the refrigerator until you are ready to use it. Do not store a mixed dose of VIRACEPT Oral Powder for more than 6 hours.

What are the possible side effects of VIRACEPT?

VIRACEPT can cause serious side effects, including:

- Diabetes and high blood sugar (hyperglycemia). Some people who take protease inhibitors including VIRACEPT can get high blood sugar, develop diabetes, or your diabetes can get worse. Some people have had to start taking medicine to treat diabetes or have had to change their diabetes medicine. Tell your healthcare provider if you notice an increase in thirst or urinate often while taking VIRACEPT.
- Increased bleeding in people with hemophilia. Some people with hemophilia have increased bleeding with protease inhibitors including VIRACEPT.
- Changes in body fat. These changes can happen in people taking HIV-1 medicines. The changes may include an increased amount of fat in the upper back and neck ("buffalo hump"), breast, and around the middle of your body (trunk). Loss of fat from the legs, arms, and face may also happen. The exact cause and long-term health effects of these conditions are not known.
- Changes in your immune system (Immune Reconstitution Syndrome) can happen when you start taking HIV-1 medicines. Your immune system may get stronger and begin to fight infections that have been hidden in your body for a long time. Call your healthcare provider right away if you start having new symptoms after starting your HIV-1 medicine.

The most common side effects of VIRACEPT in adults and adolescents (13 years of age and older) include:

- diarrhea
- nausea
- rash
- gas

The most common side effects of VIRACEPT in children (2 years of age to less than 13 years of age) include:

- diarrhea
- low white blood cell count (leukopenia and neutropenia)
- rash
- loss of appetite
- stomach-area (abdominal) pain

These are not all the possible side effects of VIRACEPT.

Call your doctor for medical advice about side effects. You may report side effects to FDA at 1-800-FDA-1088.

How should I store VIRACEPT?

- Store VIRACEPT Tablets and Oral Powder at room temperature, between 59ºF to 86ºF (15ºC to 30ºC).
- Store VIRACEPT in the original container.
- Keep the container closed tightly.

Keep VIRACEPT and all medicines out of the reach of children.

General information about the safe and effective use of VIRACEPT.

Medicines are sometimes prescribed for purposes other than those listed in a Patient Information leaflet. Do not use VIRACEPT for a condition for which it was not prescribed. Do not give VIRACEPT to other people, even if they have the same symptoms that you have. It may harm them. You can ask your pharmacist or healthcare provider for information about VIRACEPT that is written for health professionals.

What are the ingredients in VIRACEPT?

Active ingredient: nelfinavir mesylate

Tablet inactive ingredients: calcium silicate, crospovidone, magnesium stearate, hypromellose, and triacetin. In addition, the 250 mg tablet contains FD&C blue #2 powder and the 625 mg tablet contains colloidal silicon dioxide.

Oral powder inactive ingredients: microcrystalline cellulose, maltodextrin, dibasic potassium phosphate, crospovidone, hypromellose, aspartame, sucrose palmitate, and natural and artificial flavor.

VIRACEPT is a registered trademark of Agouron Pharmaceuticals, LLC
For more information, call 1-800-438-1985.
Trademarks are the property of their respective owners.
LAB-0346-15.0

This Patient Information has been approved by the U.S. Food and Drug Administration. Revised: 10/2023

PRINCIPAL DISPLAY PANEL - 250 mg Tablet Bottle Label

NDC 63010-010-30
Pfizer

VIRACEPT®
(nelfinavir mesylate)
Tablets

250 mg

ALERT: Find out about medicines that
should NOT be taken with VIRACEPT.

Note to Pharmacist: Do not cover ALERT box with
pharmacy label.

300 Tablets

Rx only

PRINCIPAL DISPLAY PANEL - 625 mg Tablet Bottle Label

NDC 63010-027-70

Pfizer

VIRACEPT®
(nelfinavir mesylate)
Tablets

625 mg

ALERT: Find out about medicines that
should NOT be taken with VIRACEPT.

Note to Pharmacist: Do not cover ALERT box with
pharmacy label.

120 Tablets

Rx only